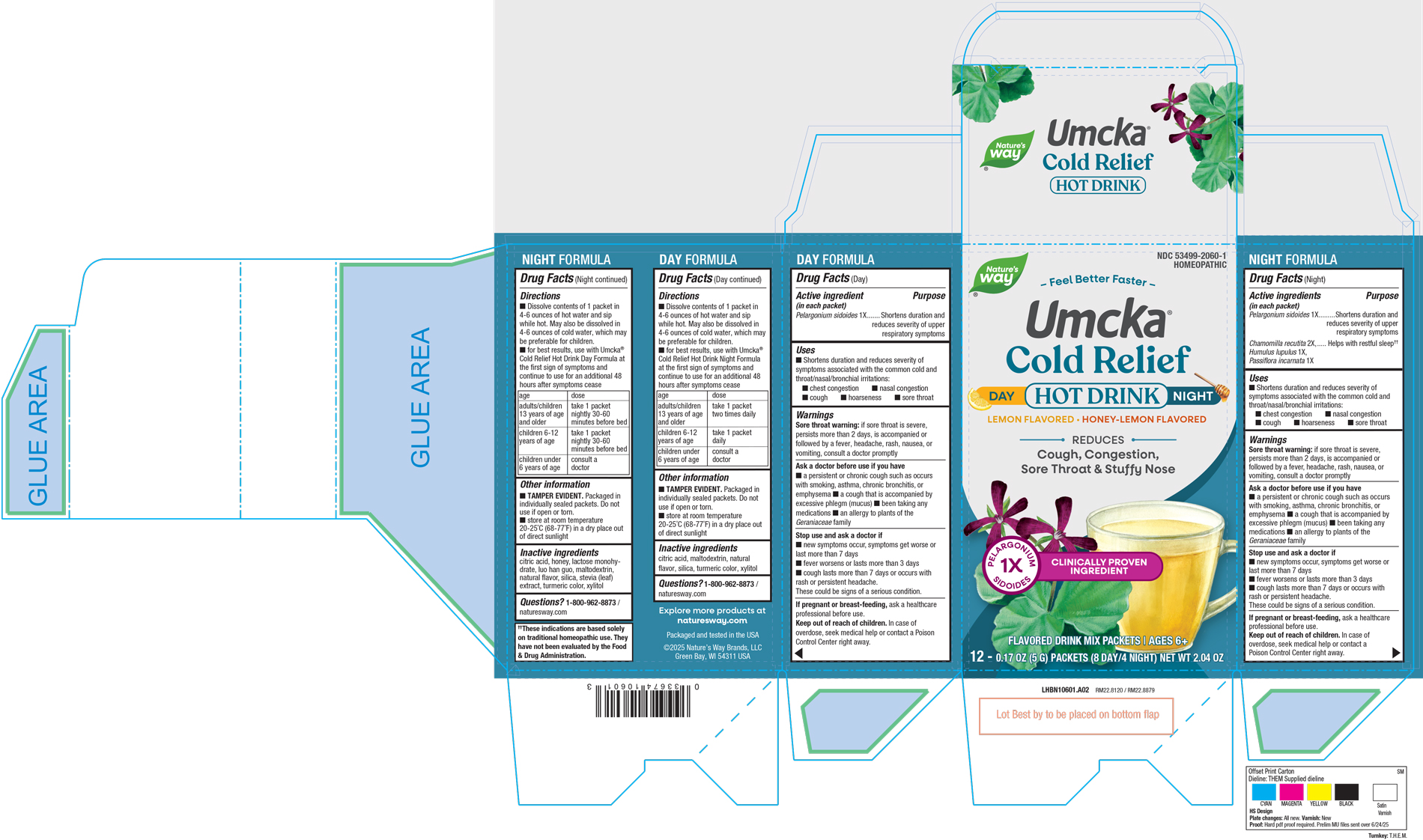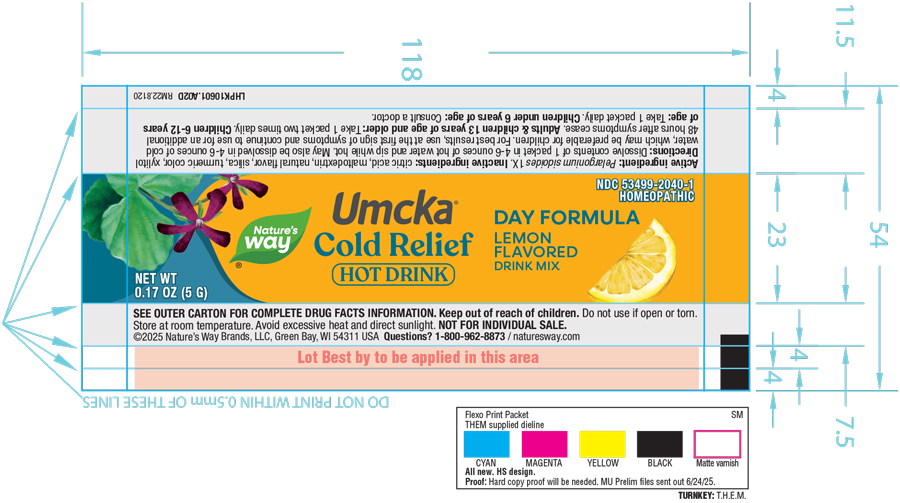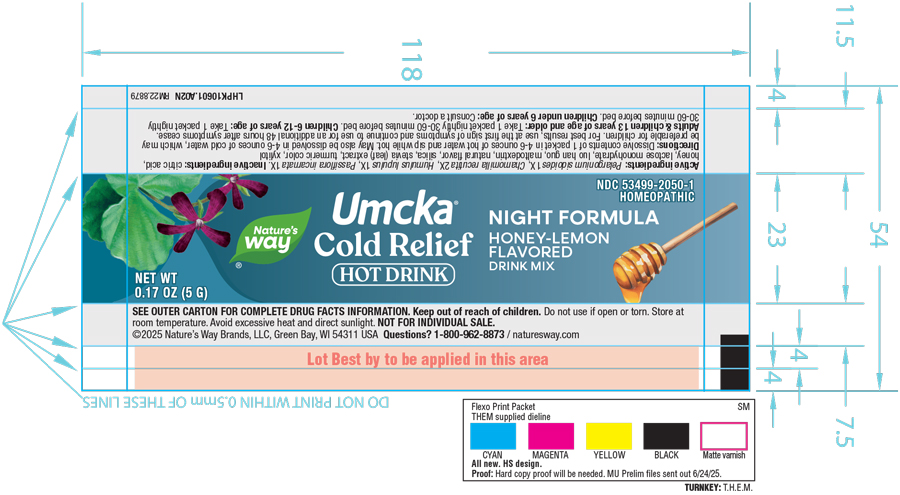 DRUG LABEL: Cold Relief
NDC: 53499-2060 | Form: KIT | Route: Oral
Manufacturer: Schwabe North America, Inc.
Category: homeopathic | Type: HUMAN OTC DRUG LABEL
Date: 20250729

ACTIVE INGREDIENTS: PELARGONIUM SIDOIDES ROOT 1 [hp_X]/5 g; PELARGONIUM SIDOIDES ROOT 1 [hp_X]/5 g; CHAMOMILE 2 [hp_X]/5 g; HUMULUS LUPULUS WHOLE 1 [hp_X]/5 g; PASSIFLORA INCARNATA WHOLE 1 [hp_X]/5 g
INACTIVE INGREDIENTS: CITRIC ACID MONOHYDRATE; MALTODEXTRIN; SILICON DIOXIDE; TURMERIC; XYLITOL; CITRIC ACID MONOHYDRATE; HONEY; LACTOSE MONOHYDRATE; SIRAITIA GROSVENORII FRUIT; MALTODEXTRIN; SILICON DIOXIDE; STEVIA LEAF; TURMERIC; XYLITOL

Cold Relief Day Plus Night

Active Ingredient

Cold Relief Day:

Pelargonium sidoides 1X

Cold Relief Night:

Pelargonium sidoides 1X

Chamomilla recutita 2X

Humulus lupulus 1X

Passiflora incarnata 1X

Inactive Ingredient

Cold Relief Day: Citric Acid, Maltodextrin, Natural Flavor, Silica, Turmeric Color, Xylitol.

Cold Relief Night: Citric Acid, Honey, Lactose Monohydrate, Lou Han Guo, Maltodextrin, Natural Flavor, Silica, Stevia Leaf Extract, Turmeric Color, Xylitol.

Dosage & Administration

Directions

Cold Relief Day: Dissolve contents of 1 packet in 4-6 ounces of hot water and sip while hot. May also be dissolved in 4-6 ounces of cold water, which may be preferable for children.

For best results, use with Umcka® Cold Relief Hot Drink Night Formula at the first sign of symptoms and continue to use for an additional 48 hours after symptoms cease.

Adults/Children 13 years of age and older: Take 1 packet two times daily

Children 6-12 years of age: Take 1 packet daily

Children under 6 years of age: Consult a doctor

Cold Relief Night: Dissolve contents of 1 packet in 4-6 ounces of hot water and sip while hot. May also be dissolved in 4-6 ounces of cold water, which may be preferable for children.

For best results, use with Umcka® Cold Relief Hot Drink Day Formula at the first sign of symptoms and continue to use for an additional 48 hours after symptoms cease.

Adults/Children 13 years of age and older: Take 1 packet nightly 30-60 minutes before bed

Children 6-12 years of age: Take 1 packet nightly 30-60 minutes before bed

Children under 6 years of age: Consult a doctor

Indications & Usage

Cold Relief Day: Shortens duration and reduces severity of symptoms associated with the common cold and throat/nasal/bronchial irritations: chest congestion, nasal congestion, cough, hoarseness, sore throat

Cold Relief Night: Shortens duration and reduces severity of symptoms associated with the common cold and throat/nasal/bronchial irritations: chest congestion, nasal congestion, cough, hoarseness, sore throat

Purpose

Cold Relief Day: Shortens duration and reduces severity of symptoms associated with the common cold and throat/nasal/bronchial irritations: chest congestion, nasal congestion, cough, hoarseness, sore throat

Cold Relief Night: Shortens duration and reduces severity of symptoms associated with the common cold and throat/nasal/bronchial irritations: chest congestion, nasal congestion, cough, hoarseness, sore throat

Warnings

Cold Relief Day: Sore throat warning: if sore throat is severe, persists more than 2 days, is accompanied or followed by a fever, headache, rash, nausea, or vomiting, consult a doctor promptly.

Cold Relief Night: Sore throat warning: if sore throat is severe, persists more than 2 days, is accompanied or followed by a fever, headache, rash, nausea, or vomiting, consult a doctor promptly.

Ask Doctor

Cold Relief Day: Ask a doctor before use if you have a persistent or chronic cough such as occurs with smoking, asthma, chronic bronchitis, or emphysema, a cough that is accompanied by excessive phlegm (mucus), been taking any medications, an allergy to plants of the Geraniaceae family.

Cold Relief Night: Ask a doctor before use if you have a persistent or chronic cough such as occurs with smoking, asthma, chronic bronchitis, or emphysema, a cough that is accompanied by excessive phlegm (mucus), been taking any medications, an allergy to plants of the Geraniaceae family.

Stop Use

Cold Relief Day: Stop use and ask a doctor if new symptoms occur, symptoms get worse or last more than 7 days, fever worsens or lasts more than 3 days, cough lasts more than 7 days or occurs with rash or persistent headache.

These could be signs of a serious condition.

Cold Relief Night: Stop use and ask a doctor if new symptoms occur, symptoms get worse or last more than 7 days, fever worsens or lasts more than 3 days, cough lasts more than 7 days or occurs with rash or persistent headache.

These could be signs of a serious condition.

Pregnancy or Breast feeding

Cold Relief Day: If pregnant or breast-feeding, ask a healthcare professional before use.

Cold Relief Night: If pregnant or breast-feeding, ask a healthcare professional before use.

Keep out of reach of children.

Cold Relief Day: Keep out of reach of children.

Cold Relief Night: Keep out of reach of children.

Overdose

Cold Relief Day: In case of overdose, seek medical help or contact a Poison Control Center right away.

Cold Relief Night: In case of overdose, seek medical help or contact a Poison Control Center right away.